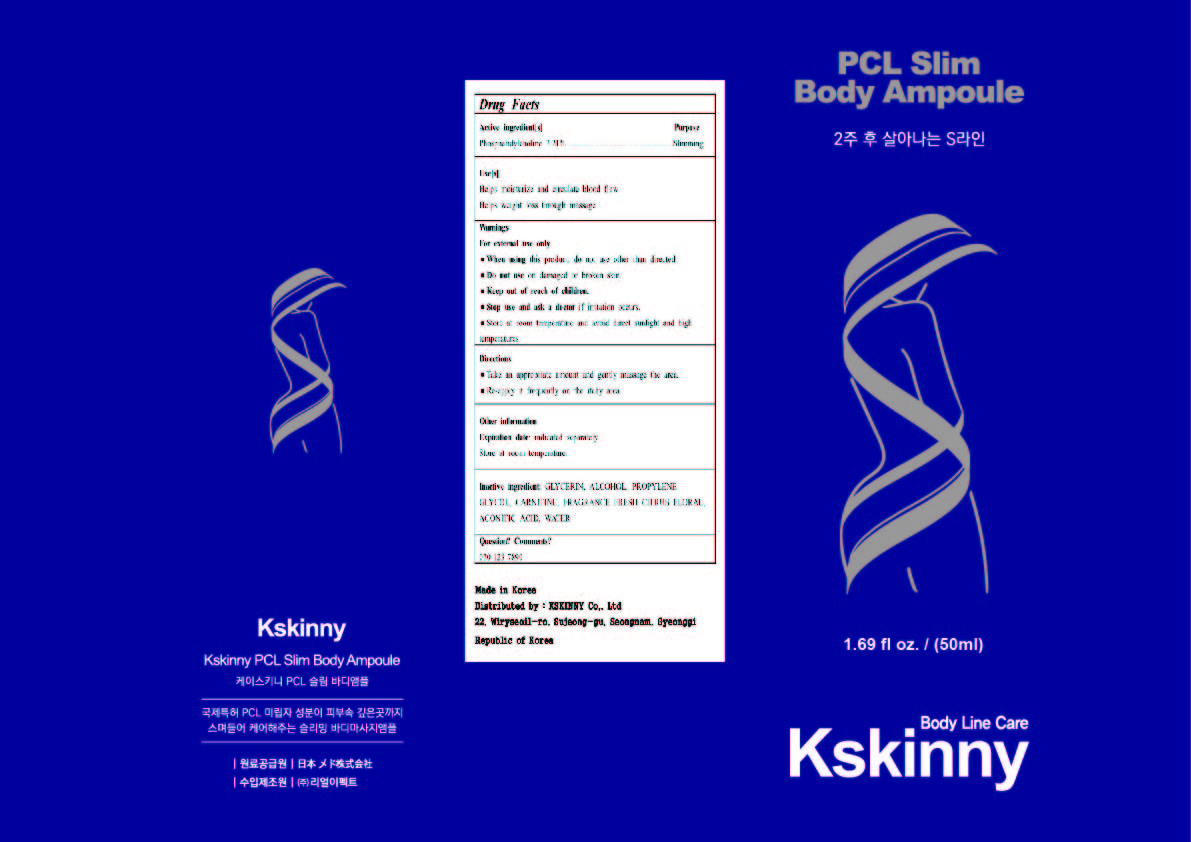 DRUG LABEL: Kskinny PCL Slim Body Ampoule
NDC: 82818-301 | Form: SOLUTION/ DROPS
Manufacturer: KSKINNY Co., Ltd
Category: otc | Type: HUMAN OTC DRUG LABEL
Date: 20230322

ACTIVE INGREDIENTS: PHOSPHATIDYLCHOLINE:CERAMIDE CHOLINEPHOSPHOTRANSFERASE 1 3.21 g/100 mL
INACTIVE INGREDIENTS: ACONITIC ACID; GLYCERIN; WATER; PROPYLENE GLYCOL; CARNITINE; FRAGRANCE FRESH CITRUS FLORAL ORC1501495; ALCOHOL

Kskinny PCL Slim Body Ampoule

Active Ingredient

Phosphatidylcholine 3.21%

Inactive Ingredients

Water, Propylene Glycol, Glycerin, Alcohol, Carnitine, Citric Acid,Fragrance

Uses

Helps moisturize and circulate blood flow

Helps weight loss through massage

Purpose

Slimming

Warnings

Stop use and ask a doctor if irritation occurs.

Warnings

Do not use on damaged or broken skin.

Warnings

When using this product, do not use other than directed.

Warnings

Keep out of reach of children.

Warnings

For external use only

Warnings

Store at room temperature and avoid direct sunlight and high temperatures.

Directions

◾ Take an appropriate amount and gently massage the area.

◾ Re-apply it frequently on the itchy area.

Questions? Comments?

070-123-7890